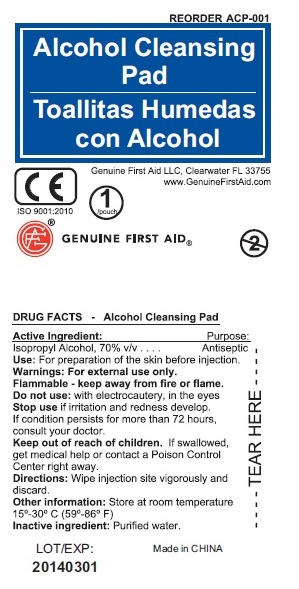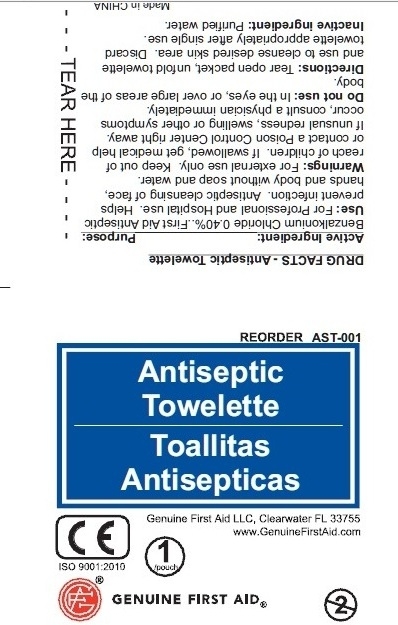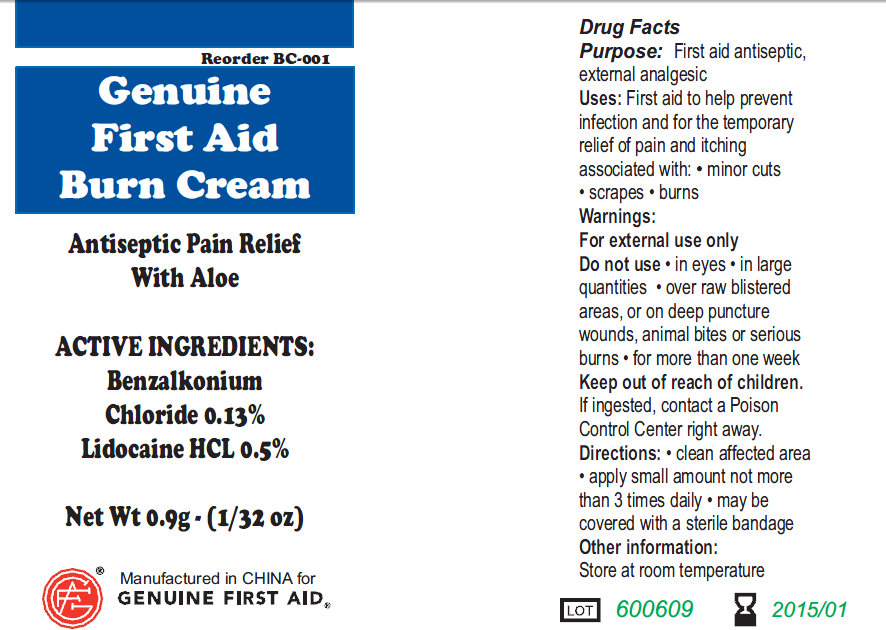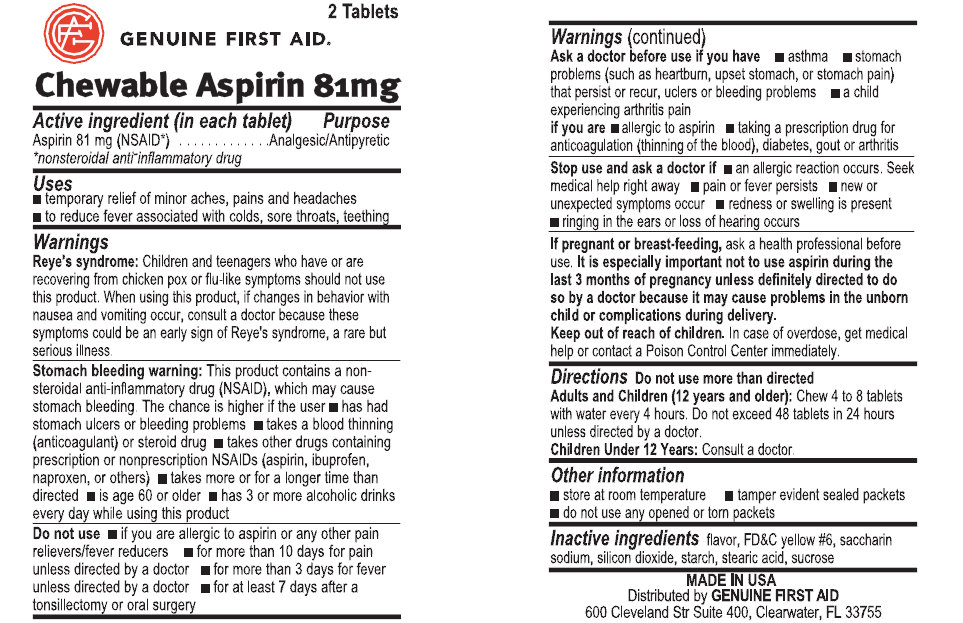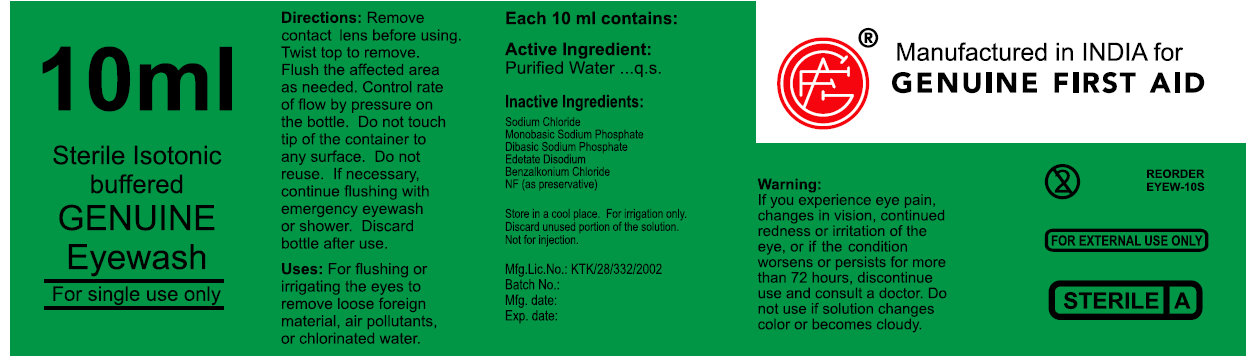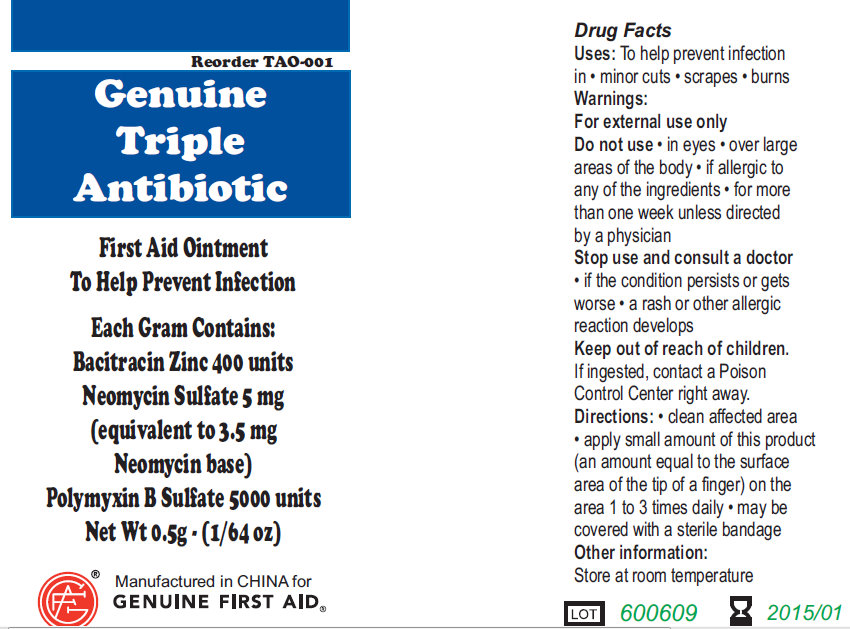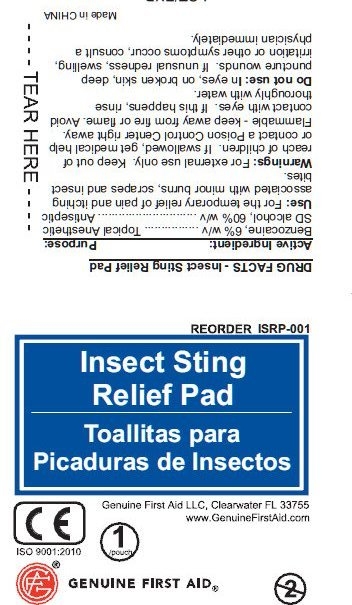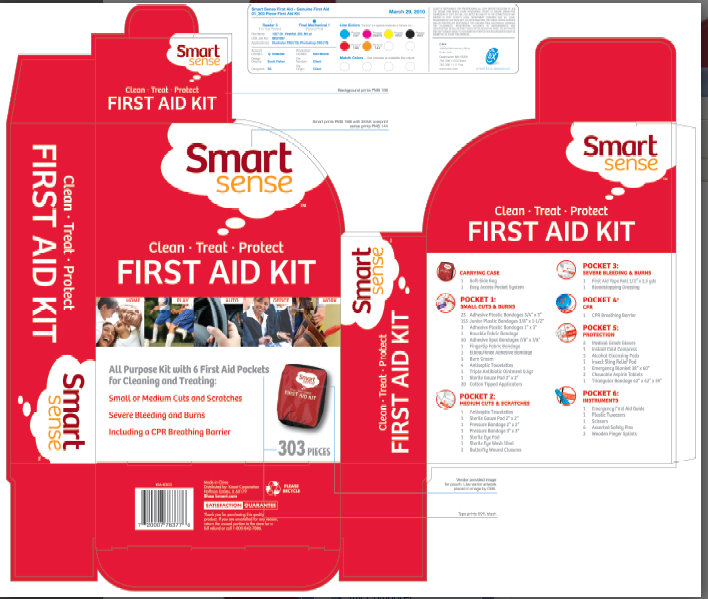 DRUG LABEL: K-Mart SmartSense First Aid Contains 303 Pieces
NDC: 49738-802 | Form: KIT | Route: TOPICAL
Manufacturer: Kmart Corporation
Category: otc | Type: HUMAN OTC DRUG LABEL
Date: 20100614

ACTIVE INGREDIENTS: BENZALKONIUM CHLORIDE 0.13 g/100 g; LIDOCAINE 0.5 g/100 g; BENZALKONIUM CHLORIDE 0.40 mL/100 mL; WATER 98.16 mL/100 mL; ISOPROPYL ALCOHOL 70 mL/100 mL; BENZOCAINE 6 mL/100 mL; ALCOHOL 60 mL/100 mL; ASPIRIN 81 mg/1 1; BACITRACIN ZINC 400 [iU]/1 g; NEOMYCIN SULFATE 5 mg/1 g; POLYMYXIN B SULFATE 5000 [iU]/1 g
INACTIVE INGREDIENTS: WATER; SODIUM CHLORIDE; SODIUM PHOSPHATE, MONOBASIC; SODIUM PHOSPHATE, DIBASIC; EDETATE DISODIUM; BENZALKONIUM CHLORIDE; WATER; FD&C YELLOW NO. 6; SACCHARIN; SODIUM CATION; SILICON DIOXIDE; STARCH, CORN; STEARIC ACID; SUCROSE

K-Mart SmartSense First Aid Contains 303 Pieces

ACTIVE INGREDIENTS:
Benzalkonium Chloride 0.13%
Lidocaine HCL 0.5%

Purpose: First aid antiseptic, external analgesic
Uses: First aid to help prevent infection and for the temporary relief of pain and itching associated with:
Minor Cuts
Scrapes
Burns

Warnings:
For external use only

Do not use: In eyes, in large quantities, over raw blistered areas, or on deep puncture wounds, animal bites or serious burns, for more than one week

Keep out of reach of Children.
If ingested, contact a Poison Control Center right away.

DOSAGE AND ADMINISTRATION

Directions: Clean affected area, Apply small amount not more than 3 times daily.
May be covered with a sterile bandage.

Other Information:
Store at room temperature

PACKAGE LABEL

Genuine First Aid Burn Cream
Antiseptic Pain Relief With Aloe
Net Wt 0.9g (1/32 oz)
Manufactured in CHINA for
Genuine First Aid.

Active Ingredient: Purpose
Benzalkonium Chloride 0.40%.......... First Aid Antiseptic

PURPOSE

Use: For Professional and Hospital use. Helps prevent infection. Antiseptic cleansing of face, hands and body without soap and water.

WARNINGS

Warning: For external use only.

Keep out of reach of children: If swallowed, get medical help or contact a Poison Control Center right away.

Stop use if unusual redness, swelling or other symptoms occur. Consult a physician immediately.

Do not use in the eyes or over large areas of the body.

WHEN USING

Directions: Tear open packet, unfold towelette and use to cleanse desired skin area. Discard towelette appropriately after single use.

Inactive Ingredient: Purified water

DESCRIPTION

LOT/EXP: Made in CHINA
20130301

PACKAGE LABEL

Antiseptic Towelette
Genuine First Aid LLC, Clearwater FL 33755
www.GenuineFirstAid.com
1/pouch
GENUINE FIRST AID

Active Ingredient: .........Bacitracin Zinc 400 units
Neomycin Sulfate 5mg (equivalent to 3.5 mg Neomycin base)
Polymyxin B Sulfate 5000 units

PURPOSE

Uses: To help prevent infection in:
minor cuts; scrapes; burns

Warnings:
For external use only.

Do not use: in eyes; over large areas of the body;
If allergic to any of the ingredients; for more than one week unless directed by a physician.

Stop use and consult a doctor:
if the condition persists or gets worse; a rash or other allergic reaction develops

Keep out of reach of children.
If ingested, contact a Poison
Control Center right away.

WHEN USING

Directions: clean affected area; apply small amount of this product (an amount equal to the surface area of the tip of a finger) on the area 1 to 3 times daily; may be covered with a sterile bandage

Other information:
Store at room temperature.

PACKAGE LABEL

Genuine Triple Antibiotic
First Aid Ointment
To Help Prevent Infection
Each Gram Contains:
Bacitracin Zinc 400 units
Neomycin Sulfate 5 mg
(equivalent to 3.5 mg
Neomycin base)
Polymyxin B Sulfate 5000 units
Net Wt. 0.5g ; (1/64 oz)
Manufactured in CHINA for
GENUINE FIRST AID.

Active Ingredient:
Purified Water USP...q.s.

Inactive Ingredients:
Sodium Chloride USP 44mg
Monobasic Sodium Phosphate USP 18mg
Sodium Phosphate Dibasic USP 111mg
Edetate Disodium USP 10mg
Benzalkonium Chloride 0.5mg
NF (as preservative)

STORAGE AND HANDLING

Store in a cool place. For irrigation only.
Discard unused portion of the solution.
Not for injection.

Warning:
If you experience eye pain, changes in vision, continued redness or irritation of the eye,
or if the condition worsens or persists for more than 72 hours, discontinue use and consult a doctor.
Do not use if solution changes color or becomes cloudy.

Directions
Remove contacts before using.
Twist top to remove.
Flush the affected area as needed. Control
Rate of flow by pressure on the bottle. Do not touch
tip of the container to any surface. Do not reuse.
If necessary continue flushing with emergency eyewash or shower.
Discard bottle after use.

Uses:
For flushing or irrigating the eyes to
remove loose foreign material, air pollutants,
or chlorinated water.

DESCRIPTION

Code No.: GUJ/DRUG/G/1080
Batch No.:
Mfg Date:
Exp: Date:

PACKAGE LABEL

10ml
Sterile Isotonic Buffered Genuine
Eyewash
For single use only

Active Ingredient: Purpose
Isopropyl Alcohol, 70% v/v............... Antiseptic

PURPOSE

Use: For preparation of skin before injection.

Warnings: For external use only.

STORAGE AND HANDLING

Flammable - keep away from fire or flame
Store at room temperature 15-30 degree Celsius (59-86 degree Fahrenheit)

Do not use: with electrocautery, in the eyes.

Stop use if irritation and redness develop. If condition persists for more than 72 hours, consult your doctor.

Keep out of reach of children. If swallowed,
get medical help or contact a Poison Control
Center right away.

WHEN USING

Wipe Injection site vigorously and discard.

Inactive Ingredient: Purified water.

DESCRIPTION

LOT/EXP: Made in CHINA
20140301

PACKAGE LABEL

Alcohol Cleansing Pad
Genuine First Aid LLC, Clearwater FL 33755
www.GenuineFirstAid.com
1/pouch
GENUINE FIRST AID

Active Ingredient: Purpose:
Benzocaine, 6% w/v.................. Topical Anesthetic
SD alcohol, 60% w/v.................. Antiseptic

PURPOSE

Use: For the temporary relief of pain and itching associated with minor burns, scrapes and insect bites.

Warnings: For external use only.
Avoid contact with eyes. If this happens, rinse thoroughly with water.

Keep out of reach of children. If swallowed, get medical help or contact a Poison Control Center right away.

STORAGE AND HANDLING

Flammable - keep away from fire or flame.

Do not use: In eyes, on broken skin, deep puncture wounds. If unusual redness, swelling, irritation or other symptoms occur, consult a physician immediately.

DESCRIPTION

Made in CHINA
LOT/EXP:

PACKAGE LABEL

Insect Sting Relief Pad
Genuine First Aid LLC, Clearwater FL 33755
www.GenuineFirstAid.com
1/pouch
GENUINE FIRST AID

Active ingredient (in each tablet) Purpose
Aspirin 81 mg (NSAID*). . . . . . . . . . . . . Analgesic/Antipyretic
*nonsteroidal anti-inflammatory drug

Uses
temporary relief of minor aches, pains and headaches
to reduce fever associated with colds, sore throats, teething

Warnings
Reye's syndrome: Children and teenagers who have or are recovering from chicken pox or flu-like symptoms should not use this product. When using this product, if changes in behavior with nausea and vomiting occur, consult a doctor because these symptoms could be an early sign of reye's syndrome, a rare but serious illness.
Stomach bleeding warning: This product contains a non-steroidal anti-inflammatory drug (NSAID), which may cause stomach bleeding. The chance is higher if the user; has had stomach ulcers or bleeding problems takes a blood thinning (anticoagulant) or steroid drug takes other drugs containing prescription or nonprescription NSAIDs (aspirin, ibuprofen, naproxen, or others) takes more or for a longer time than directed is age 60 or older has 3 or more alcoholic drinks every while using this product.

Do not use
if you are allergic to aspirin or any other pain relievers/fever reducers
for more than 10 days for pain unless directed by a doctor
for more than 3 days for fever unless directed by a doctor
for at least 7 days after a tonsillectomy or oral surgery

Ask a doctor before use if you have;
asthma
stomach problems (such as heartburn, upset stomach, or stomach pain) that persist or recur, ulcers or bleeding problems
a child experiencing arthritis pain
if you are;
allergic to aspirin
taking prescription drug for anticoagulation (thinning of blood), diabetes, gout or arthritis

Stop use and ask a doctor if;
an allergic reaction occurs, Seek medical help right away
pain or fever persists
new or unexpected symptoms occur
redness or swelling is present
ringing in ears or loss of hearing occurs

PREGNANCY OR BREAST FEEDING

If pregnant or breast-feeding, ask a health professional before use. It is especially important not to use aspirin during the last 3 months of pregnancy unless definitely directed to do so by a doctor because it may cause problems in unborn child or complications during delivery.

Keep out of reach of children. In case of overdose, get medical help or contact a Poison Control Center immediately.

DOSAGE AND ADMINISTRATION

Directions Do not use more than directed
Adults and Children (12 years and older): Chew 4 to 8 tablets with water every 4 hours, Do not exceed 48 tablets in 24 hours unless directed by a doctor.
Children Under 12 years: Consult a doctor.

STORAGE AND HANDLING

Store at room temperature
tamper evident sealed packets
do not use any opened or torn packets

INACTIVE INGREDIENT

Inactive ingredients flavor, FD and C yellow No. 6, saccharin, sodium, silicon dioxide, starch, stearic acid, sucrose

DESCRIPTION

MADE IN USA
Distributed by GENUINE FIRST AID
600 Cleveland Str Suite 400, Clearwater, FL 33755

PACKAGE LABEL

2 Tablets
GENUINE FIRST AID.
Chewable Aspirin 81mg

PACKAGE LABEL

SmartSense

Clean Treat Protect
FIRST AID KIT

HOME PLAY AUTO OFFICE WORK

All Purpose Kit with 6 First Aid Pockets for Cleaning and Treating:

Small or Medium Cuts and Scratches
Severe Bleeding and Burns
Including a CPR Breather Barrier
303 PIECES

CARRYING CASE

1 Soft-side Bag
1 Easy Access Pocket System

POCKET 1:
SMALL CUTS AND BURNS
25 Adhesive Plastic Bandages 3/4"x3"
155 Junior Plastic Bandages 3/8"x1-1/2"
3 Adhesive Plastic Bandages 1"x3"
1 Knuckle Fabric Bandage
50 Adhesive Spot Bandages 7/8"x7/8"
1 Fingertip Fabric Bandage
1 Elbow/Knee Adhesive Bandage
1 Burn Cream
4 Antiseptic Towelettes
1 Triple Antibiotic Ointment 0.5gr
1 Sterile Gauge Pads 2"x2"
20 Cotton Tipped Applicators

POCKET 2:
MEDIUM CUTS AND SCRATCHES
4 Antiseptic Towelettes
1 Sterile Gauze Pad 2"x2"
1 Pressure Bandage 2"X2"
1 Pressure Bandage 3"X3"
1 Sterile Eye Pads
1 Sterile Eye Wash 10ml
2 Butterfly Wound Closures

POCKET 3:
SEVERE BLEEDING AND SCRATCHES
1 First Aid Tape Roll 1/2"x2.5 yds.
1 Bloodstopper Dressing

POCKET 4:
CPR
1 CPR Breathing Barrier

POCKET 5
PROTECTION
2 Medical Grade Gloves
1 Instant Cold Compress
5 Alcohol Cleansing Pads
1 Insect Sting Relief Pads
1 Emergency Blanket 38"x60"
2 Chewable Aspirin Tablets
1 Triangular Bandage 42"x42"x59"

POCKET 6:
INSTRUMENTS
1 Emergency First Aid Guide
1 Plastic Tweezers
1 Scissors
6 Assorted Safety Pins
2 Wooden Finger Splints

KM-R303
Made in China
Distributed by: Kmart Corporation
Hoffman Estates, IL 60179
Shop kmart.com
PLEASE RECYCLE
SATISFACTION GUARANTEE
Thank you for purchasing this quality product. If you are unsatisfied for any reason, return the unused portion to the store for a full refund or call 1-800-842-7886.